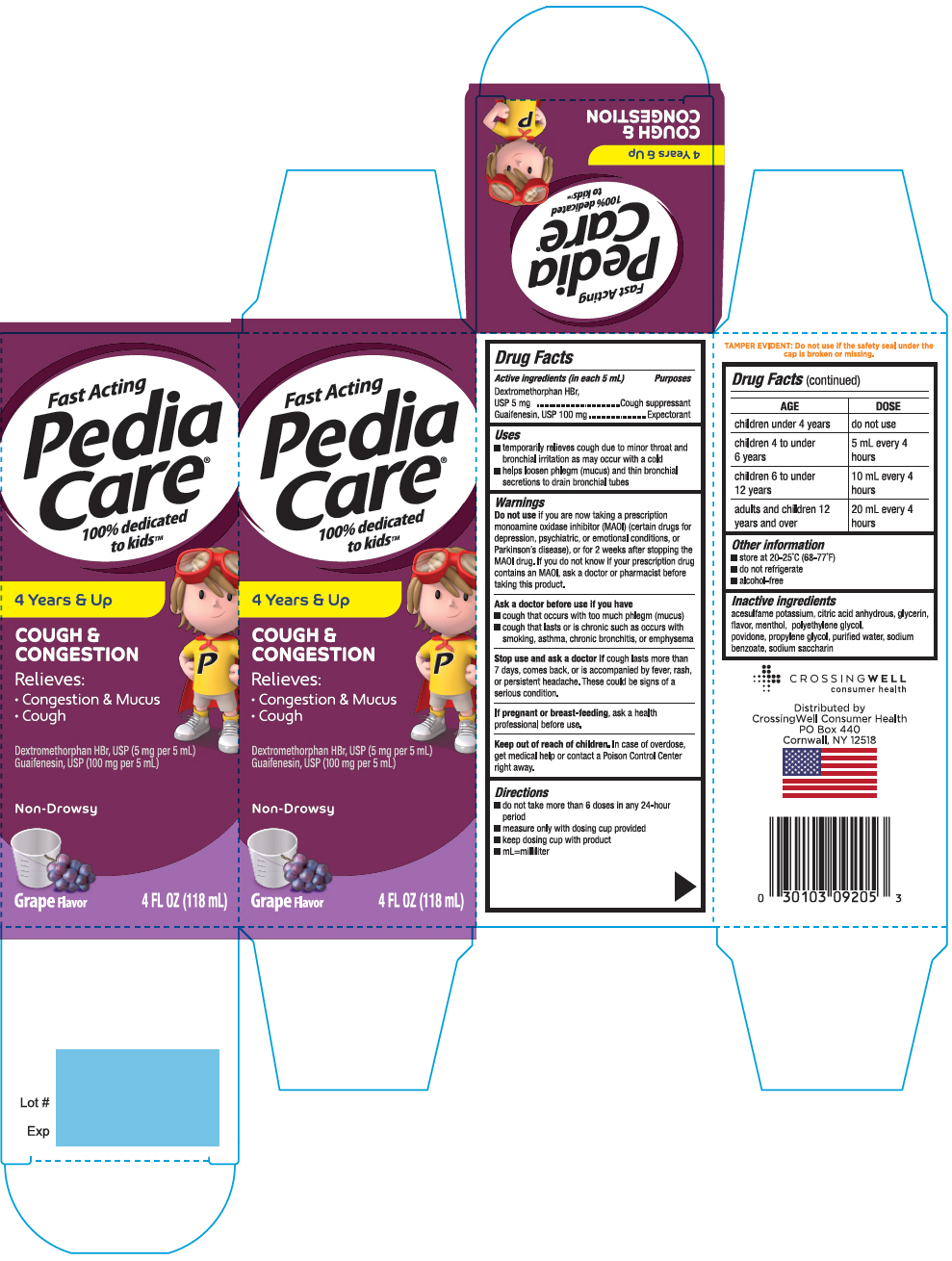 DRUG LABEL: Pediacare Childrens Cough and Congestion Grape
NDC: 52412-992 | Form: SYRUP
Manufacturer: RANDOB LABS,LTD. DBA CROSSINGWELL CONSUMER HEALTH
Category: otc | Type: HUMAN OTC DRUG LABEL
Date: 20241230

ACTIVE INGREDIENTS: DEXTROMETHORPHAN HYDROBROMIDE 5 mg/5 mL; GUAIFENESIN 100 mg/5 mL
INACTIVE INGREDIENTS: ACESULFAME POTASSIUM; CITRIC ACID MONOHYDRATE; GLYCERIN; MENTHOL, UNSPECIFIED FORM; POLYETHYLENE GLYCOL, UNSPECIFIED; POVIDONE, UNSPECIFIED; PROPYLENE GLYCOL; WATER; SODIUM BENZOATE; SACCHARIN SODIUM

Pediacare®Children's Cough and Congestion Grape

Drug Facts

ACTIVE INGREDIENT

PURPOSE

Active ingredients (in each 5 mL) | Purposes
Dextromethorphan HBr, USP 5 mg | Cough suppressant
Guaifenesin, USP 100 mg | Expectorant

Uses

- temporarily relieves cough due to minor throat and bronchial irritation as may occur with a cold
- helps loosen phlegm (mucus) and thin bronchial secretions to drain bronchial tubes

Warnings

DO NOT USE

Do not useif you are now taking a prescription monoamine oxidase inhibitor (MAOI) (certain drugs for depression, psychiatric, or emotional conditions, or Parkinson's disease), or for 2 weeks after stopping the MAOI drug. If you do not know if your prescription drug contains an MAOI, ask a doctor or pharmacist before taking this product.

Ask a doctor before use if you have

- cough that occurs with too much phlegm (mucus)
- cough that lasts or is chronic such as occurs with smoking, asthma, chronic bronchitis, or emphysema

Stop use and ask a doctor ifcough lasts more than 7 days, comes back, or is accompanied by fever, rash, or persistant headache. These could be signs of a serious condition.

PREGNANCY OR BREAST FEEDING

If pregnant or breast-feeding,ask a health professional before use.

Keep out of reach of children.In case of overdose, get medical help or contact a Poison Control Center right away.

Directions

- do not take more than 6 doses in any 24-hour period
- measure only with dosing cup provided
- keep dosing cup with product
- mL=milliliter

AGE | DOSE
children under 4 years | do not use
children 4 to under 6 years | 5 mL every 4 hours
children 6 to under 12 years | 10 mL every 4 hours
adults and children 12 years and over | 20 mL every 4 hours

Other information

- store at 20-25°C (68-77°F)
- do not refrigerate
- alcohol-free

Inactive ingredients

acesulfame potassium, citric acid anhydrous, glycerin, flavor, menthol, polyethylene glycol, povidone, propylene glycol, purified water, sodium benzoate, sodium saccharin

Distributed by
CrossingWell Consumer Health
PO Box 440
Cornwall, NY 12518

PRINCIPAL DISPLAY PANEL - 118 mL Bottle Carton

Fast Acting

Pedia
Care®

100% dedicated
to kids™

4 Years & Up

COUGH &
CONGESTION

Relieves:

- Congestion & Mucus
- Cough

Dextromethorphan HBr, USP (5 mg per 5 mL)
Guaifenesin, USP (100 mg per 5 mL)

Non-Drowsy

Grape Flavor

4 FL OZ (118 mL)